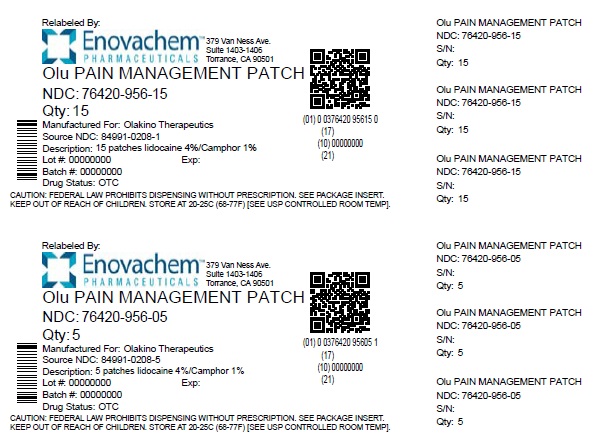 DRUG LABEL: Olu Pain Management
NDC: 76420-956 | Form: PATCH
Manufacturer: Asclemed USA, Inc.
Category: otc | Type: HUMAN OTC DRUG LABEL
Date: 20250401

ACTIVE INGREDIENTS: CAMPHOR (NATURAL) 0.01 g/1 g; LIDOCAINE 0.04 g/1 g
INACTIVE INGREDIENTS: TARTARIC ACID; WATER; BOSWELLIA SERRATA WHOLE; METHYLPARABEN; SODIUM POLYACRYLATE (8000 MW); PROPYLENE GLYCOL; DIHYDROXYALUMINUM AMINOACETATE; GLYCERIN; ASCORBIC ACID; ALPHA-TOCOPHEROL; ALCOHOL; ARNICA MONTANA FLOWER

Olu Pain Management Patch

ACTIVE INGREDIENTS

Lidocaine 4%

PURPOSE

Local Anesthetic

ACTIVE INGREDIENTS

Camphor 1%

PURPOSE

Counterirritant

USES

For the temporary relief of muscle pain and joint pain associated with:

-Backache -Cramps -Soreness -Strains -Discomfort -Neckache

WARNINGS:

FOR EXTERNAL USE ONLY

ALLERGY ALERT

Local anesthetics may cause methemoglobinemia. If an allergic reaction occurs, stop use and seek medical attention immediately.

DO NOT USE

-On damaged, irritated, or infected skin

-With a bandage or heating pad

-If you are allergic to any ingredients in this product

-In the eyes, nose, or mouth

-Otherwise as directed

WHEN USING THIS PRODUCT

Avoid contact with the eyes, nose, and mouth

STOP USE AND ASK DOCTOR IF

-Any of the warnings apply to you

-Excessive skin irritation develops

-Condition worsens

-Symptoms persist for more than 7 days, or symptoms clear up and occur again within 3 days

IF PREGNANT OR BREASTFEEDING

Ask a healthcare professional before use

KEEP OUT OF REACH OF CHILDREN

If ingested, seek medical help or contact Poison Control immediately

FLAMMABLE

Keep away from excessive heat or open flame

DIRECTIONS

Adults and Children 12 Years of Age and Older:

-Clean and dry the affected area

-Apply gel pad directly onto skin for up to 12 hours

-Wash hands immediately after use

-Gel pad can be cut into pieces and used on up to 2 body parts at a time

-One application per day is recommended

OTHER INFORMATION

-Store in a cool, dry place with pouch tightly closed. Keep from freezing.

-If the tamper-evident foil seal is not intact, do not use

INACTIVE INGREDIENTS

Arnica Extract, Boswellia Extract, Vitamin C, Vitamin E, Ethyl Alcohol, Propylene Glycol, Glycerol, Sodium Polyacrylate, Tartaric Acid, Dihydroxyaluminium Aminoacetate, Methylparaben, Water

QUESTIONS OR COMMENTS

info@olakinotherapeutics.com

Relabeled by:

Enovachem PHARMACEUTICALS

Torrance, CA 90501